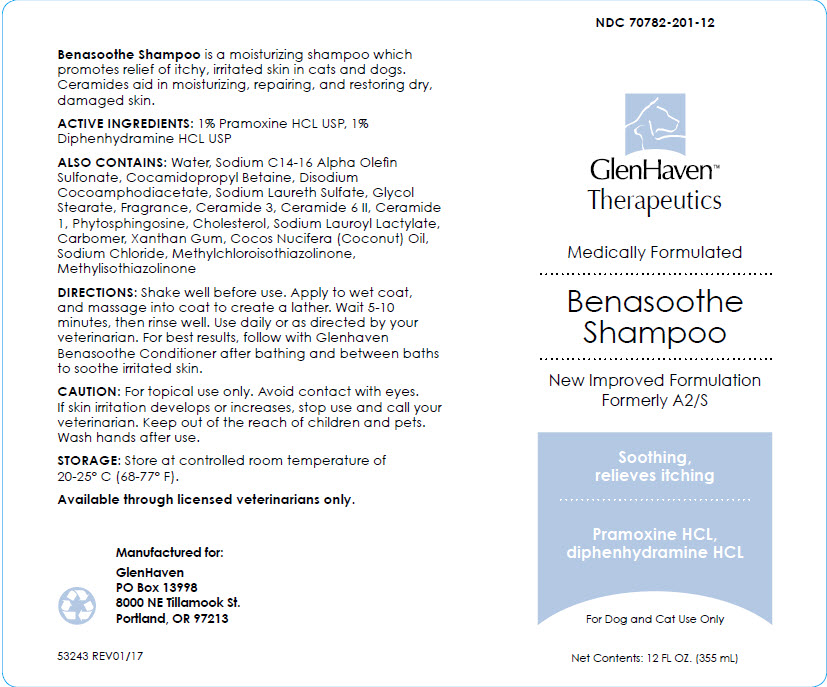 DRUG LABEL: GlenHaven Benasoothe
NDC: 70782-201 | Form: SHAMPOO
Manufacturer: GlenHaven LLC
Category: animal | Type: OTC ANIMAL DRUG LABEL
Date: 20211209

ACTIVE INGREDIENTS: PRAMOXINE HYDROCHLORIDE 10 mg/1 mL; DIPHENHYDRAMINE HYDROCHLORIDE 10 mg/1 mL

GlenHaven™ Benasoothe Shampoo

VETERINARY INDICATIONS

Benasoothe Shampoo is a moisturizing shampoo which promotes relief of itchy, irritated skin in cats and dogs. Ceramides aid in moisturizing, repairing, and restoring dry, damaged skin.

DESCRIPTION

ACTIVE INGREDIENTS: 1% Pramoxine HCL USP, 1% Diphenhydramine HCL USP

ALSO CONTAINS: Water, Sodium C14-16 Alpha Olefin Sulfonate, Cocamidopropyl Betaine, Disodium Cocoamphodiacetate, Sodium Laureth Sulfate, Glycol Stearate, Fragrance, Ceramide 3, Ceramide 6 II, Ceramide 1, Phytosphingosine, Cholesterol, Sodium Lauroyl Lactylate, Carbomer, Xanthan Gum, Cocos Nucifera (Coconut) Oil, Sodium Chloride, Methylchloroisothiazolinone, Methylisothiazolinone

DOSAGE AND ADMINISTRATION

DIRECTIONS: Shake well before use. Apply to wet coat, and massage into coat to create a lather. Wait 5-10 minutes, then rinse well. Use daily or as directed by your veterinarian. For best results, follow with Glenhaven Benasoothe Conditioner after bathing and between baths to soothe irritated skin.

WARNINGS

CAUTION: For topical use only. Avoid contact with eyes. If skin irritation develops or increases, stop use and call your veterinarian. Keep out of the reach of children and pets. Wash hands after use.

HOW SUPPLIED

STORAGE AND HANDLING

STORAGE: Store at controlled room temperature of 20-25° C (68-77° F).

Available through licensed veterinarians only.

Manufactured for:
GlenHaven
PO Box 13998
8000 NE Tillamook St.
Portland, OR 97213

53243 REV01/17

PRINCIPAL DISPLAY PANEL - 355 mL Bottle Label

NDC 70782-201-12

GlenHaven™
Therapeutics

Medically Formulated

Benasoothe
Shampoo

New Improved Formulation
Formerly A2/S

Soothing,
relieves itching

Pramoxine HCL,
diphenhydramine HCL

For Dog and Cat Use Only

Net Contents: 12 FL OZ. (355 mL)